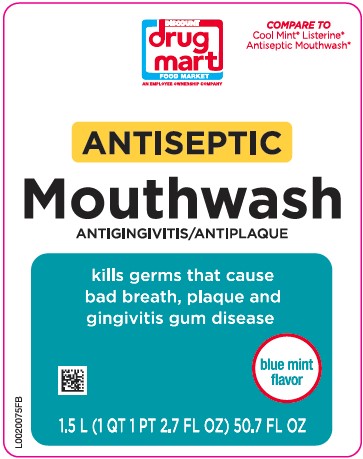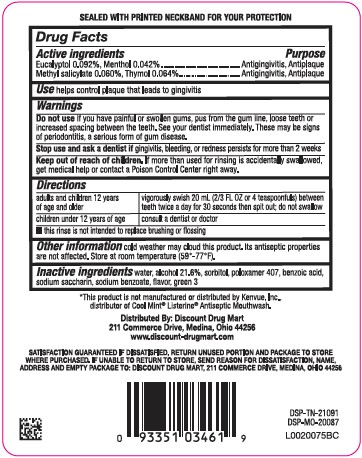 DRUG LABEL: Antispetic
NDC: 53943-756 | Form: MOUTHWASH
Manufacturer: Discount Drug Mart
Category: otc | Type: HUMAN OTC DRUG LABEL
Date: 20260204

ACTIVE INGREDIENTS: EUCALYPTOL 0.92 mg/1 mL; MENTHOL 0.42 mg/1 mL; METHYL SALICYLATE 0.6 mg/1 mL; THYMOL 0.64 mg/1 mL
INACTIVE INGREDIENTS: WATER; ALCOHOL; SORBITOL; POLOXAMER 407; BENZOIC ACID; SACCHARIN SODIUM; SODIUM BENZOATE; FD&C GREEN NO. 3

Discount Drug Mart 664.003/664AT rev 2-AU
Antiseptic Mouth Rinse

Tamper Evident Statement

SEALED WITH PRINTED NECKBAND FOR YOUR PROTECTION

Active ingredients

Eucalyptol 0.092%

Menthol 0.042%

Methyl salicylate 0.060%

Thymol 0.064%

Purpose

Antigingivitis, Antiplaque

Use

helps control plaque that leads to gingivitis

Warnings

for this product

Do not use

if you have painful or swollen gums, pus from the gum line, loose teeth or increased spacing between the teeth. See your dentist immediately. These may be signs of periodontitis, a serious form of gum disease.

Stop use and ask a dentist if

gingivitis, bleeding, or redness persists for more than 2 weeks.

Keep out of reach of children.

If more than used for rinsing is accidentally swallowed, get medical help or contact a Poison Control Center right away.

Directions

adults and children 12 years of age and older - vigorously swish 20 mL (2/3 FL OZ or 4 teaspoonfuls) between teeth twice a day for 30 seconds then spit out; do not swallow

children under 12 years of age - consult a dentist or doctor

- this rinse is not intended to replace brushing or flossing

Other information

cold weather may cloud this product. Its antiseptic properties are not affected. Store at room temperature (59°-77°F).

Inactive ingredients

water, alcohol 21.6%, sorbitol, poloxamer 407, benzoic acid, sodium saccharin, sodium benzoate, flavor, FD&C green no.3

Disclaimer

*This product is not manufactured or distributed by Kenvue, Inc., distributor of Cool Mint® ListerineAntiseptic Mouthwash.

ADVERSE REACTION

Distributed By: Discount Drug Mart

211 Commerce Drive, Medina, Ohio 44256

www.discount-drugmart.com

SATISFACTION GUARANTEED IF DISSATISFIED, RETURN UNUSED PORTION AND PACKAGE TO STORE WHERE PURCHASED. IF UNABLE TO RETURN TO STORE, SEND REASON FOR DISSATISFACTION, NAME, ADDRESS AND EMPTY PACKAGE TO DISCOUNT DRUG MART, 11 COMMERCE DRIVE, MEDINA, OHIO 44256

DSP-TN-21091

DSP-MO-20087

principal display panel

DISCOUNT DRUG MART FOOD MARKET

AN EMPLOYEE OWNERSHIP COMPANY

COMPARE TO COOL MINT® LISTERINE® ANTISEPTIC MOUTHWASH*

ANTISEPTIC

MOUTHWASH

ANTIGINGIVITIS/ANTIPLAQUE

klils germs that cause bad breath, plaque and gingivitis gum disease

blue mint flavor

1.5 L (1 QT 1 PT 2.7 FL OZ) 50.7 FL OZ